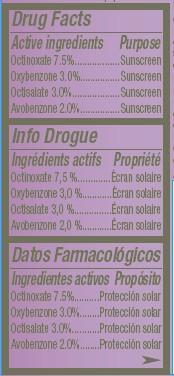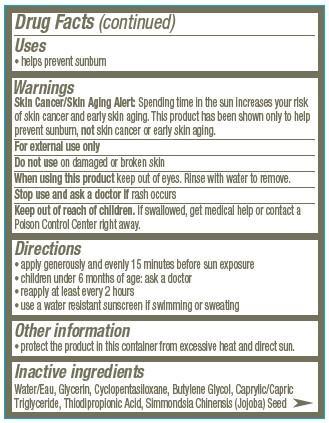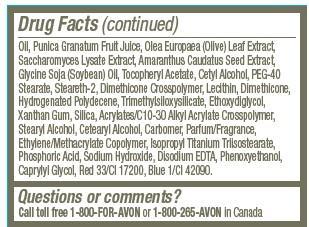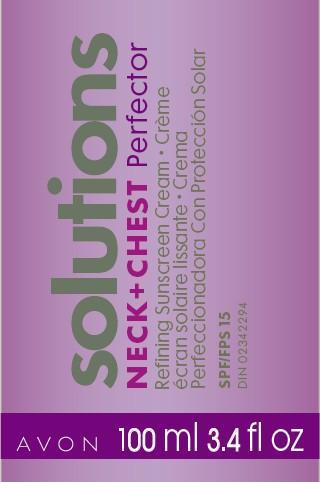 DRUG LABEL: Solutions
NDC: 10096-0206 | Form: CREAM
Manufacturer: Avon Products, Inc.
Category: otc | Type: HUMAN OTC DRUG LABEL
Date: 20130210

ACTIVE INGREDIENTS: OCTINOXATE 75 mg/1 mL; OXYBENZONE 30 mg/1 mL; OCTISALATE 30 mg/1 mL; AVOBENZONE 20 mg/1 mL

Active ingredients
Octinoxate 7.5%...............
Oxybenzone 3.0%............
Octisalate 3.0%................
Avobenzone 2.0%.............

Purpose
........Sunscreen
........Sunscreen
........Sunscreen
......Sunscreen

Uses
• helps prevent sunburn

Warnings
Skin Cancer/Skin Aging Alert: Spending time in the sun increases your risk of skin cancer and early skin aging. This product has been shown only to help prevent sunburn, not skin cancer or early skin aging.
For external use only

Do not use on damaged or broken skin

When using this product keep out of eyes. Rinse with water to remove.

Stop use and ask a doctor if rash occurs

Keep out of reach of children. If swallowed, get medical help or contact a Poison Control Center right away.

Directions
• apply generously and evenly 15 minutes before sun exposure
• children under 6 months of age: ask a doctor
• reapply at least every 2 hours
• use a water resistant sunscreen if swimming or sweating

Other information
• protect the product in this container from excessive heat and direct sun.

Inactive ingredients
Water/Eau, Glycerin, Cyclopentasiloxane, Butylene Glycol, Caprylic/Capric Triglyceride, Thiodipropionic Acid, Simmondsia Chinensis (Jojoba) Seed Oil, Punica Granatum Fruit Juice, Olea Europaea (Olive) Leaf Extract, Saccharomyces Lysate Extract, Amaranthus Caudatus Seed Extract, Glycine Soja (Soybean) Oil, Tocopheryl Acetate, Cetyl Alcohol, PEG-40 Stearate, Steareth-2, Dimethicone Crosspolymer, Lecithin, Dimethicone, Hydrogenated Polydecene, Trimethylsiloxysilicate, Ethoxydiglycol, Xanthan Gum, Silica, Acrylates/C10-30 Alkyl Acrylate Crosspolymer, Stearyl Alcohol, Cetearyl Alcohol, Carbomer, Parfum/Fragrance, Ethylene/Methacrylate Copolymer, Isopropyl Titanium Triisostearate, Phosphoric Acid, Sodium Hydroxide, Disodium EDTA, Phenoxyethanol, Caprylyl Glycol, Red 33/CI 17200, Blue 1/CI 42090.

Questions or comments?
Call toll free 1-800-FOR-AVON or 1-800-265-AVON in Canada